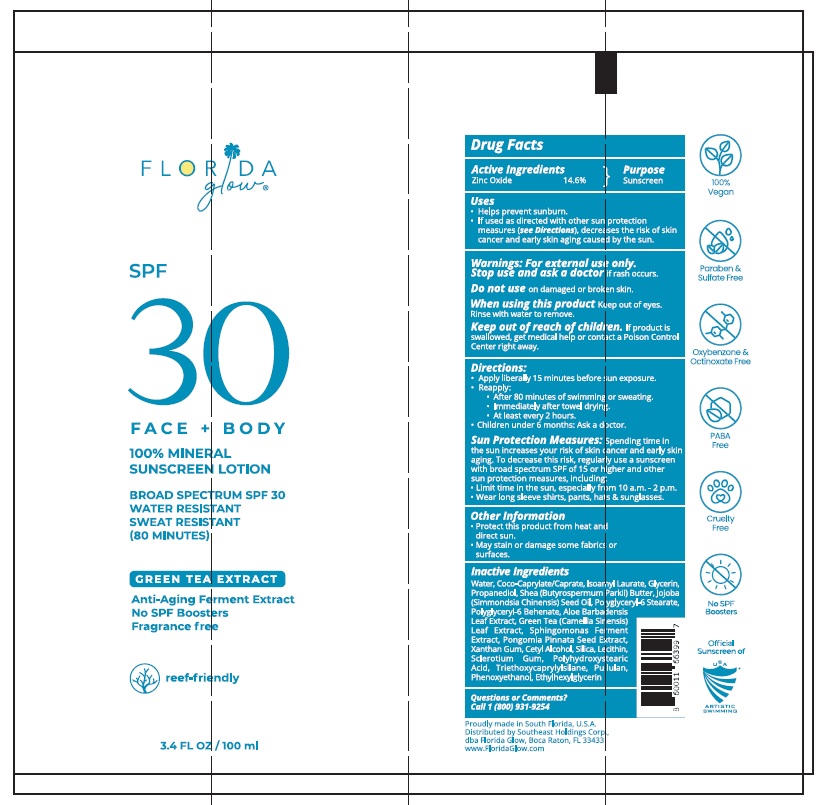 DRUG LABEL: Florida Glow SPF 30
NDC: 83862-005 | Form: LOTION
Manufacturer: Southeast Holdings Corp.
Category: otc | Type: HUMAN OTC DRUG LABEL
Date: 20251112

ACTIVE INGREDIENTS: ZINC OXIDE 14.6 g/100 mL
INACTIVE INGREDIENTS: TRIETHOXYCAPRYLYLSILANE; WATER; COCOYL CAPRYLOCAPRATE; ISOAMYL LAURATE; GLYCERIN; POLYGLYCERYL-6 STEARATE; JOJOBA OIL; PROPANEDIOL; SHEA BUTTER; XANTHAN GUM; PHENOXYETHANOL; GREEN TEA LEAF; CETYL ALCOHOL; SILICON DIOXIDE; POLYHYDROXYSTEARIC ACID (2300 MW); PONGAMIA PINNATA SEED; SPHINGOFUNGIN C; ALOE VERA LEAF JUICE; SOYBEAN LECITHIN; BETASIZOFIRAN; PULLULAN; ETHYLHEXYLGLYCERIN

Active Ingredients

Zinc Oxide 14.6%

Purpose

Sunscreen

Uses

- Helps prevent sunburn
- If used as directed with other sun protection measures (see Directions), decreases the risk of skin cancer and early skin aging caused by the sun.

Warnings

For external use only.

Stop use and ask a doctorif rash occurs.

Do not useon damaged or broken skin.

When using this productKeep out of eyes.Rinse with water to remove.

Keep out of reach of children. If product is swallowed, get medical help or contact a Poison Control Center right away.

Directions

Apply liberally 15 minutes before sun exposure
• Reapply:
• After 80 minutes of swimming or sweating
• Immediately after towel drying
• at least every 2 hours.
• Children under 6 months: Ask a doctor.
Sun Protection Measures. Spending time in the sun increases your risk of skin cancer and early skin aging. To decrease this risk, regularly use a sunscreen with Broad Spectrum of 15 or nigher and other sun protection measures, including:
• limit time in the sun, espec1ally from 10 a.m.- 2 p.m.
• wear long sleeve shirts, pants, hats & sunglasses

Inactive Ingredients

Triethoxycaprylylsilane, Water, Coco-Caprylate/Caprate, Isoamyl laurate, Glycerine, Polyglyceryl -6 Stearate, Jojoba Oil, Propanadiol, Shea Butter, Xanthum Gum, Phenoxyethanol, Green Tea Leaf Extract, Cetyl Alcohol, Silica, Polyhydroxystearic Acid, Pongomia Pinnata Seed Extract, Sphingomonas Ferment Extract, Aloe Barbadensis Leaf Extract, Lecithin, Sclerotium Gum, Pullulan, Ethylhexylglycerin

Other Information

- Protect this product from heat and direct sun.
- May stain or damage some fabrics or surfaces.

Questions or Comments?
Call 1 (800) 931-9254